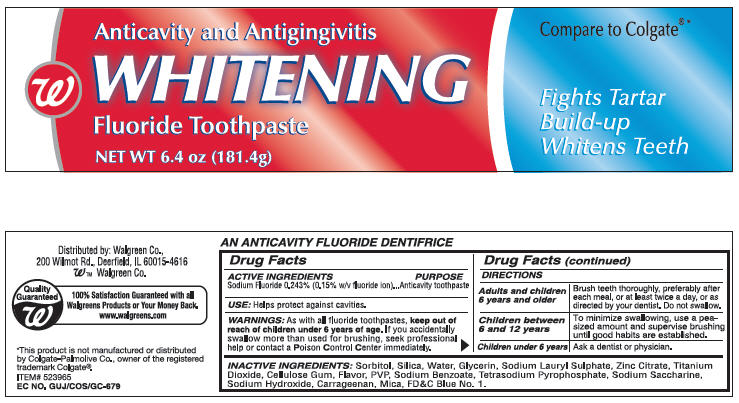 DRUG LABEL: Walgreens Anticavity and Antigingivits Whitening Fluoride Toothpaste
NDC: 67659-062 | Form: PASTE, DENTIFRICE
Manufacturer: Team Technologies, Inc
Category: otc | Type: HUMAN OTC DRUG LABEL
Date: 20091105

ACTIVE INGREDIENTS: Sodium Fluoride 2.43 mg/1 g
INACTIVE INGREDIENTS: Sorbitol; SILICON DIOXIDE; Water; Glycerin; SODIUM LAURYL SULFATE; Zinc Citrate; Titanium Dioxide; CROSCARMELLOSE SODIUM; SODIUM BENZOATE; SODIUM PYROPHOSPHATE; SACCHARIN SODIUM; SODIUM HYDROXIDE; Carrageenan; FD&C BLUE NO. 1

Walgreens Anticavity and Antigingivitis Whitening Fluoride Toothpaste

ACTIVE INGREDIENTS

Sodium Fluoride 0.234% (0.15% w/v fluoride ion..........................Anticavity toothpaste

Use:

Helps protect against cavities.

WARNINGS

As with all fluoride toothpastes, keep out of reach of children under 6 years of age. If you accidentally swallow more than used for brushing, seek professional help or contact the Poison Control Center immediately.

DOSAGE AND ADMINISTRATION

Adults and children 6 years or older | Brush Teeth throughly, preferably after each meal, or at least twice a day, or as directed by your dentist. Do not swallow
Children between 6 and 12 years | To minimize swallowing, use a pea-sized amount and supervise brushing until good habits are established.
Children under 6 years | Ask a dentist or physician.

Inactive Ingredients

Sorbitol, Silica, Water, Glycerin, Sodium Laurel Sulphate, Zinc Citrate, Titanium Dioxide, Cellulose Gum, Flavor, PVP, Sodium Benzoate, Tetrasodium Pyrophosphate, Sodium Saccharine, Sodium Hydroxide, Carrageenan, Mica, FDC Blue No. 1.

Principal Display Panel

Anticavity and Antigingivitis Compare to Colgate

WHITENING

Fluoride Toothpaste Fights Tartar

Build-up
NET WT 6.4 oz (181.4 g) Whitens Teeth